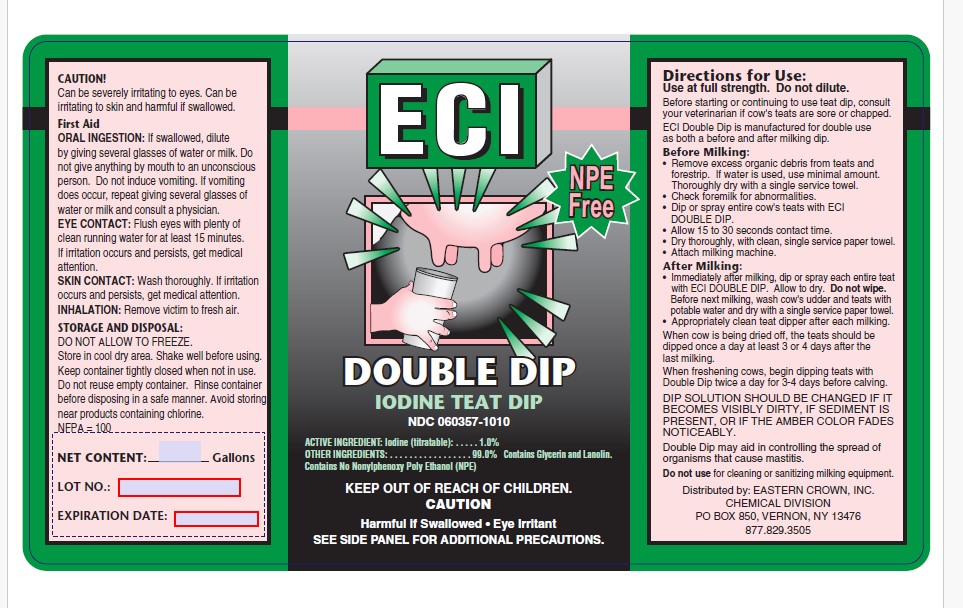 DRUG LABEL: Double Dip
NDC: 60357-1010 | Form: SOLUTION
Manufacturer: Eastern Crown Inc.
Category: animal | Type: OTC ANIMAL DRUG LABEL
Date: 20240926

ACTIVE INGREDIENTS: IODINE 10 g/1 L
INACTIVE INGREDIENTS: GLYCERIN; LANOLIN; WATER

ECI Double Dip Iodine Teat Dip

DIRECTIONS FOR USE

Use at full strength. Do not dilute.

Before starting or continuing to use teat dip, consult your veterinarian if cow's teats are sore or chapped.

ECI Double Dip is manufactured for double use as both a before and after milking dip.

Before Milking:

- Remove excess organic debris from teats and forestrip. If water is used, use minimal amount. Thoroughly dry with a single service towel.
- Check foremilk for abnormalities.
- Dip or spray entire cow's teats with ECI DOUBLE DIP.
- Allow 15 to 30 seconds contact time.
- Dry thoroughly, with clean, single service paper towel.
- Attach milking machine

After Milking:

- Immediately after milking, dip or spray each entire teat with ECI DOUBLE DIP. Allow to dry. Do not wipe. Before next milking, wash cow's udder and teats with potable water and dry with a single service paper towel.
- Appropriately clean teat dipper after each milking.

When cow is being dried off, the teats should be dipped once a day at least 3 or 4 days after the last milking.

When freshening cows, begin dipping teats with Double Dip twice a day for 3-4 days before calving.

DIP SOLUTION SHOULD BE CHANGED IF IT BECOMES VISIBLY DIRTY, IF SEDIMENT IS PRESENT, OR IF THE AMBER COLOR FADES NOTICEABLY.

Double Dip may aid in controlling the spread of organisms that cause mastitis.

Do not use for cleaning or sanitizing milking equipment.

STORAGE AND DISPOSAL:

DO NOT ALLOW TO FREEZE.

Store in cool dry area. Shake well before using. Keep container tightly closed when not in use. Do not reuse empty container. Rinse container before disposing in a safe manner. Avoid storing near products coontaining chlorine.

NFPA = 100

CAUTION!

Can be severely irritating to eyes. Can be irritating to skin and harmful if swallowed.

First Aid

ORAL INGESTION: If swallowed, dilute by giving several glasses of water or milk. Do not give anything by mouth to an unconscious person. Do not induce vomiting. If vomiting does occur, repeat giving several glasses of water or milk and consult a physician.

EYE CONTACT: Flush eyes with plenty of clean running water for at least 15 minutes. If irritation occurs and persists, get medical attention.

SKIN CONTACT: Wash thoroughly. If irritation occurs and persists, get medical attention.

INHALATION: Remove victim to fresh air.